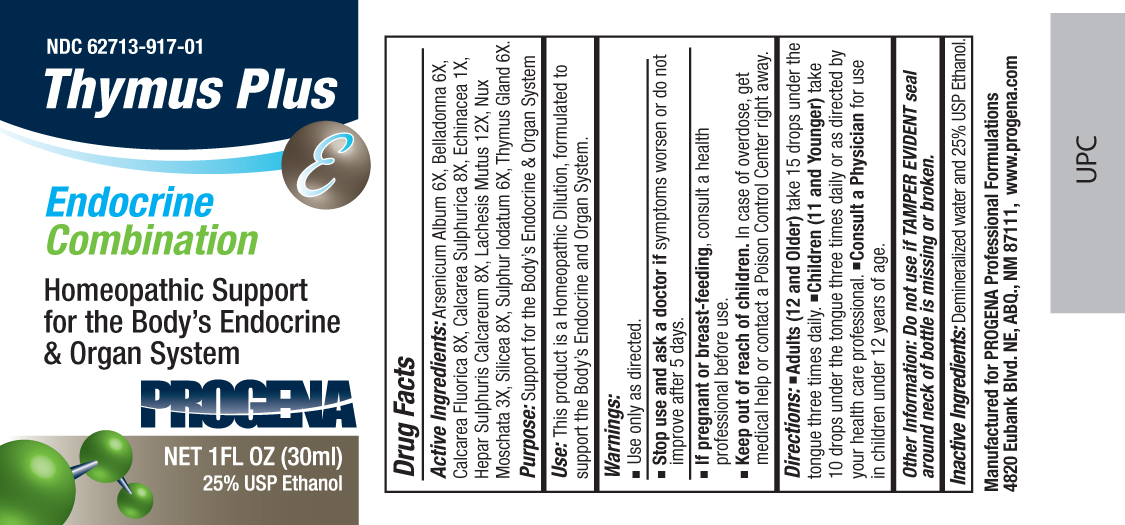 DRUG LABEL: Progena
NDC: 62713-917 | Form: LIQUID
Manufacturer: Meditrend, Inc. DBA Progena Professional Formulations
Category: homeopathic | Type: HUMAN OTC DRUG LABEL
Date: 20151207

ACTIVE INGREDIENTS: ARSENIC TRIOXIDE 6 [hp_X]/1 mL; ATROPA BELLADONNA 6 [hp_X]/1 mL; CALCIUM FLUORIDE 8 [hp_X]/1 mL; CALCIUM SULFATE ANHYDROUS 8 [hp_X]/1 mL; ECHINACEA ANGUSTIFOLIA 1 [hp_X]/1 mL; CALCIUM SULFIDE 8 [hp_X]/1 mL; LACHESIS MUTA VENOM 12 [hp_X]/1 mL; NUTMEG 3 [hp_X]/1 mL; SILICON DIOXIDE 8 [hp_X]/1 mL; SULFUR IODIDE 6 [hp_X]/1 mL; SUS SCROFA THYMUS 6 [hp_X]/1 mL
INACTIVE INGREDIENTS: WATER; ALCOHOL

Thymus Plus

ACTIVE INGREDIENT

Active Ingredients:Arsenicum Album 6X, Belladonna 6X, Calcarea Fluorica 8X, Calcarea Sulphurica 8X, Echinacea 1X, Hepar Sulphuris Calcareum 8X, Lachesis Mutus 12X, Nux Moschata 3X, Silicea 8X, Sulphur Iodatum 6X, Thymus Gland 6X.

PURPOSE

Purpose:Support for the Body's Endocrine and Organ System

INDICATIONS AND USAGE

Use:This product is a Homeopathic Dilution, formulated to support the Body's Endocrine and Organ System.

Keep Out of Reach of Children. In case of overdose, get medical help or contact a
Poison Control Center right away.

Warnings:

- Use Only as directed.
- Stop use and ask a doctor ifsymptoms worsen or do not improve after 5 days.
- If pregnant or breast-feeding, consult a health professional before use.

DOSAGE AND ADMINISTRATION

Directions:• Adults (12 and Older)take 15 drops under the tongue three times daily.• Children (11 and Younger)take 10 drops under the tongue three times daily or as directed by your health care professional.• Consult a Physicianfor use in children under 12 years of age.

Other Information: Do not use if TAMPER EVIDENT seal around neck of bottle is missing or broken.

INACTIVE INGREDIENT

Inactive Ingredients:USP Purified Water and 25% USP Ethanol.

PACKAGE LABEL

Manufactured for Progena Professional Formulations
4820 Eubank Blvd. NE, ABQ, NM 87111, www.progena.com